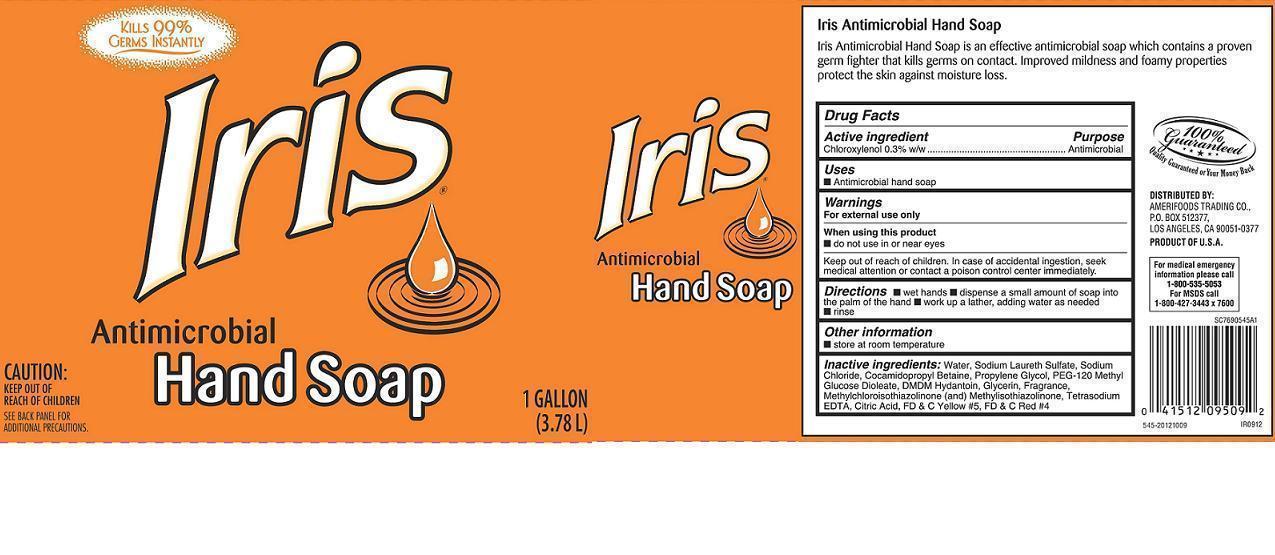 DRUG LABEL: IRIS ANTIMICROBIAL HAND
NDC: 59860-545 | Form: SOAP
Manufacturer: SMART AND FINAL STORES
Category: otc | Type: HUMAN OTC DRUG LABEL
Date: 20131015

ACTIVE INGREDIENTS: CHLOROXYLENOL 3 g/1000 mL
INACTIVE INGREDIENTS: WATER; SODIUM LAURETH SULFATE; PROPYLENE GLYCOL; METHYLCHLOROISOTHIAZOLINONE; METHYLISOTHIAZOLINONE; COCAMIDOPROPYL BETAINE; PEG-120 METHYL GLUCOSE DIOLEATE; DMDM HYDANTOIN; GLYCERIN; EDETATE SODIUM; CITRIC ACID MONOHYDRATE; SODIUM CHLORIDE

Active ingredient

Chloroxylenol 0.3% w/w

Purpose

Antimicrobial

Keep out of reach of children

In case of accidental ingestion, seek medical attention or contact a poison control center immediately.

Uses

- Antimicrobial hand soap

Warnings

For external use only

When using this product

- do not use in or near eyes

Directions

 wet hands  dispense a small amount of soap into the palm of the hand.  work up a lather, adding water as needed.  rinse.

Other information

 store at room temperature

Inactive ingredients:

Water, Sodium laureth sulfate, Sodium chloride, Cocamidopropyl betaine, PEG-120 Methyl glucose dioleate, DMDM hydantoin, Propylene glycol, Methylchloroisothiazolinone, Methylisothiazolinone, Fragrance, Tetrasodium EDTA, Glycerin, Citric acid, FD&C Yellow #5, FD&C Red #4.